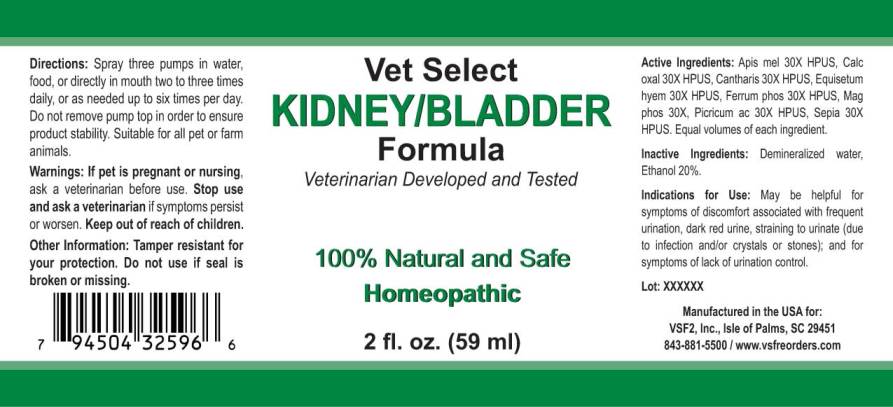 DRUG LABEL: Kidney/Bladder
NDC: 86100-0002 | Form: LIQUID
Manufacturer: Vsf2, Inc.
Category: homeopathic | Type: OTC ANIMAL DRUG LABEL
Date: 20251110

ACTIVE INGREDIENTS: APIS MELLIFERA 30 [hp_X]/1 mL; CALCIUM OXALATE MONOHYDRATE 30 [hp_X]/1 mL; LYTTA VESICATORIA 30 [hp_X]/1 mL; EQUISETUM HYEMALE 30 [hp_X]/1 mL; FERROSOFERRIC PHOSPHATE 30 [hp_X]/1 mL; MAGNESIUM PHOSPHATE, DIBASIC TRIHYDRATE 30 [hp_X]/1 mL; PICRIC ACID 30 [hp_X]/1 mL; SEPIA OFFICINALIS JUICE 30 [hp_X]/1 mL
INACTIVE INGREDIENTS: WATER; ALCOHOL

Drug Facts:

ACTIVE INGREDIENTS:

Apis Mellifica 30X HPUS, Calcarea Oxalica 30X HPUS, Cantharis 30X HPUS, Equisetum Hyemale 30X HPUS, Ferrum Phosphoricum 30X HPUS, Magnesia Phosphorica 30X HPUS, Picricum Acidum 30X HPUS, Sepia 30X HPUS.

Equal volumes of each ingredient.

INDICATIONS FOR USE:

May be helpful for symptoms of discomfort associated with frequent urination, dark red urine, straining to urinate (due to infection and/or crystals or stones); and for symptoms of lack of urination control.

WARNINGS:

If pet is pregnant or nursing, ask a veterinarian before use.

Stop use and ask a veterinarian if symptoms persist or worsen.

Keep out of reach of children.

Other Information: Tamper resistant for your protection. Do not use if seal is broken or missing.

KEEP OUT OF THE REACH OF CHILDREN:

Keep out of reach of children.

DIRECTIONS:

Spray three pumps in water, food or directly in mouth two to three times daily, or as needed up to six times per day. Do not remove pump top in order to ensure product stability. Suitable for all pet or farm animals.

INDICATIONS FOR USE:

May be helpful for symptoms of discomfort associated with frequent urination, dark red urine, straining to urinate (due to infection and/or crystals or stones); and for symptoms of lack of urination control.

INACTIVE INGREDIENTS:

Demineralized water, Ethanol 20%.

QUESTIONS:

Manufactured in the USA for:

VSF2, Inc., Isle of Palms, SC 29451

843-881-5500 / www.vsfreorders.com

PACKAGE LABEL DISPLAY:

Vet Select

KIDNEY/BLADDER

Formula

Veterinarian Developed and Tested

100% Natural and Safe

Homeopathic

2 fl. oz. (59 ml)